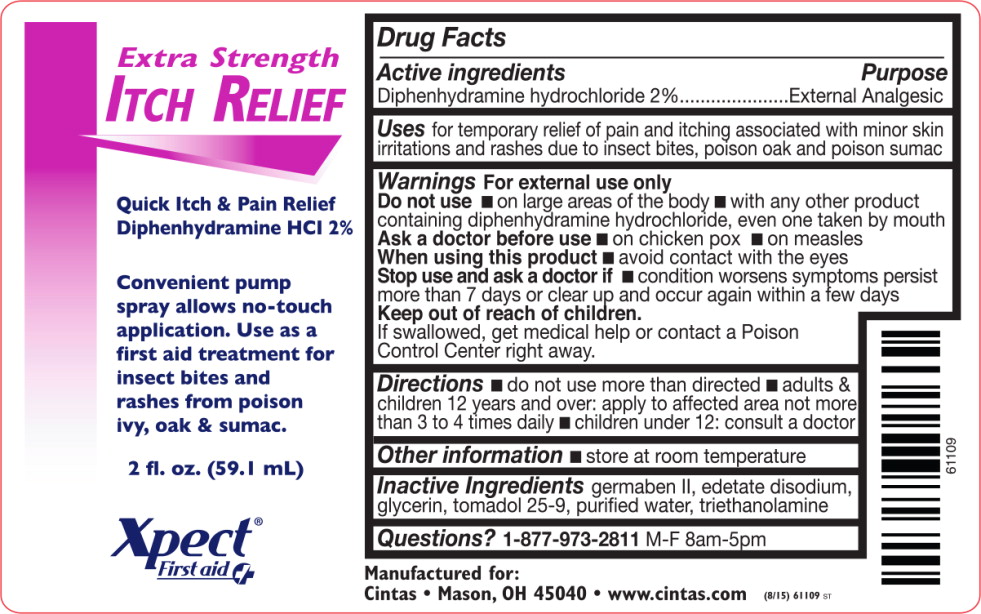 DRUG LABEL: Itch Relief
NDC: 68421-8300 | Form: LIQUID
Manufacturer: Cintas First Aid & Safety
Category: otc | Type: HUMAN OTC DRUG LABEL
Date: 20150903

ACTIVE INGREDIENTS: diphenhydramine hydrochloride 20.3 g/1 L
INACTIVE INGREDIENTS: diazolidinyl urea; edetate disodium; glycerin; C12-15 PARETH-9; water; trolamine

Respond ITCH RELIEF SPRAY
Itch Relief Spray

Drug Facts

Active Ingredients

Diphenhydramine hydrochloride 2%

Purpose

External Analgesic

Uses:

For the temporary relief of pain and itching associated with minor skin irritations and rashes due to insect bites, poison oak and poison sumac.

Warnings

For external use only

Do not use

- on large areas of the body
- with any other product containing diphenhydramine hydrochloride, even one taken by mouth

Ask a doctor before use

- on chicken pox
- on measles

When using this product

- avoid contact with the eyes

Stop use and ask doctor if

- condition worsens
- symptoms persist more than 7 days or clear up and occur again within a few days

Keep out of reach of children If swallowed, get medical help or contact a Poison Control Center right away.

Directions:

- do not use more than directed
- adults & children12 and over: apply to affected area not more than 3 to 4 times daily
- children under 12 years: consult a doctor

Inactive Ingredients

germaben II, edetate disodium, glycerin, tomadol 25-9, purified water, triethanolamine

Principal Display Panel - Bottle Label

Extra Strength
Itch Relief

Quick Itch & Pain Relief
Diphenhydramine HCl 2%

Convenient pump
spray allows no-touch
application. Use as a
first aid treatment for
insect bites and
rashes from poison
ivy, oak & sumac.

2 fl. oz. (59.1 mL)

Xpect®

First aid